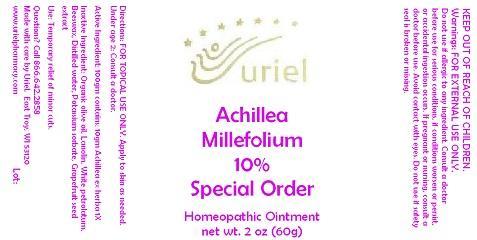 DRUG LABEL: Achillea Millefolium 10 Special Order
NDC: 48951-1253 | Form: OINTMENT
Manufacturer: Uriel Pharmacy Inc.
Category: homeopathic | Type: HUMAN OTC DRUG LABEL
Date: 20141117

ACTIVE INGREDIENTS: ACHILLEA MILLEFOLIUM 1 [hp_X]/1 g
INACTIVE INGREDIENTS: OLIVE OIL; LANOLIN; PETROLATUM; YELLOW WAX; WATER; POTASSIUM SORBATE; CITRUS PARADISI SEED

Achillea Millefolium 10 Special Order

INDICATIONS AND USAGE

Directions: FOR TOPICAL USE ONLY.

DOSAGE AND ADMINISTRATION

Apply to skin as needed. Under age 2: Consult a doctor.

Active Ingredient: 100gm contains: 10gm Achillea ex herba 1X

Inactive Ingredient: Organic olive oil, Lanolin, White petrolatum, Beeswax, Distilled water, Potassium sorbate, Grapefruit seed extract

PURPOSE

Use: Temporary relief of minor cuts.

KEEP OUT OF REACH OF CHILDREN.

WARNINGS

Warnings: FOR EXTERNAL USE ONLY. Do not use if allergic to any ingredient. Consult a doctor before use for serious conditions, if conditions worsen or persist, or accidental ingestion occurs. If pregnant or nursing, consult a doctor before use. Avoid contact with eyes. Do not use if safety seal is broken or missing.

QUESTIONS

Questions? Call 866.642.2858 Made with care by Uriel, East Troy, WI 53120 www.urielpharmacy.com